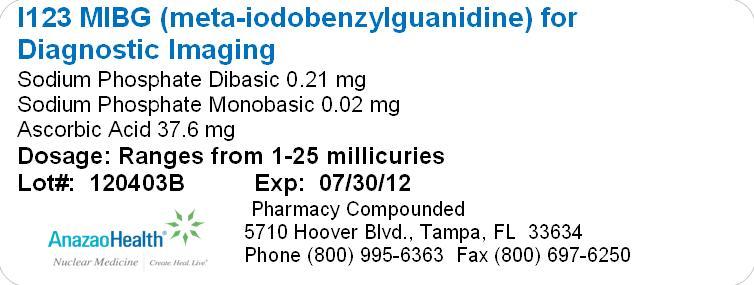 DRUG LABEL: i 123 MIBG
NDC: 51808-103 | Form: INJECTION, POWDER, LYOPHILIZED, FOR SOLUTION
Manufacturer: AnazaoHealth Corporation
Category: prescription | Type: HUMAN PRESCRIPTION DRUG LABEL
Date: 20120523

ACTIVE INGREDIENTS: IOBENGUANE SULFATE I-123 25 mCi/1 1
INACTIVE INGREDIENTS: SODIUM PHOSPHATE, DIBASIC 0.21 mg/1 1; SODIUM PHOSPHATE, MONOBASIC, MONOHYDRATE 0.02 mg/1 1; ASCORBIC ACID 37.6 mg/1 1

I-123 MIBG

Description

I-123 MIBG is provided as a freeze-dried, radio-labeled sterile powder. The powder is reconstituted with 2 mL of sterile normal saline. The dose should be measured using a dose calibrator prior to administration. Caution: Radioactive Material. A commonly used name for iobenguane is meta-iodobenzylguanidine or MIBG.

Clinical Pharmacology

Iobenguane or meta-iodobenzylguanidine (MIBG) is a physiological analog of the guanidines, such as guanethidine and phenethylguanidine. In adrenergic nerves, guanidines are believed to share the same transport pathway as norepinephrine and to accumulate in, and displace norepinephrine from, intraneuronal storage granules. Similarly, I-123 MIBG is concentrated in, stored in, and released from chromaffin granules. The retention of I-123 MIBG in the adrenal medulla may be a result of their uptake in adrenergic neurons and subsequent sequestration into chromaffin storage granules. Due to their selective uptake mechanism, I-123 MIBG allows specific detection and localization of neuroendocrine tumors and adrenal medullary hyperplasia. The gamma emissions given off by I-123 MIBG allow detection of adrenergic tumors by scintigraphy. Medullary thyroid carcinoma: Although the mechanism of I-123 MIBG uptake by medullary thyroid carcinoma (MTC) is not completely understood, it has been found that MTC can produce catecholamines (epinephrine and norepinephrine). Therefore, I-123 MIBG could be taken up and stored in catecholamine vesicles of MTC.

Indications and Usage

Iobenguane is indicated as a radioactive isotope diagnosing for adrenomedullary disorders and neuroendocrine tumors.

Tumors, adrenal medulla (diagnosis): I-123 MIBG is used for diagnostic imaging of the adrenal medulla, for the evaluation and localization of intra- and extra-adrenal pheochromocytomas, paragangliomas, and neuroblastomas, as well as for localization of metastatic lesions from these tumors. I-123 MIBG can also be used for confirmation of diagnosis of pheochromocytoma when catecholamine determination tests are unclear.

Tumors, carcinoid (diagnosis): I-123 MIBG scintigraphy is used as screening procedures for suspected carcinoid tumors, especially those of intestinal origin.

Hyperplasia, adrenal medulla (diagnosis): I-123 MIBG is used in the evaluation of the adrenal medulla for disorders such as medullary hyperplasia in patients at risk of developing medullary disease (e.g., multiple endocrine neoplasia [MEN type 2, MEN type 3]).

Carcinoma, thyroid (diagnosis): I-123 MIBG is used for diagnostic imaging of medullary thyroid carcinoma.

DISTRIBUTION

After intravenous administration, there is rapid uptake of MIBG mainly in the liver, and in lesser amounts in the lungs, heart, and salivary glands. A limited number of patients may show activity in normal adrenals, lung, skeletal, muscle, and blocked thyroid glands. Although the uptake in normal adrenal glands is very low, hyperplastic adrenals and tumors such as pheochromocytoma, neuroblastoma, and other tumors with neurosecretory granules have a relatively higher uptake. Significant clearance of I-123 MIBG from the liver and the spleen occurs within 72 hours. I-123 MIBG—In adrenal medullary tumors: Initial images may be obtained 2 to 3 hours after injection. Images may also be obtained at 18 to 24 hours, and as late as 48 hours post injection. Most pheochromocytomas are visualized at 24 hours. However, due to the short half-life of I-123 MIBG, images may not be possible at times when background (e.g., liver) activity is low and imaging would be optimal. Small amounts of radioactivity used in diagnosis; radiation received is low and considered safe.

ELIMINATION

Renal; about 40 to 50% of the injected activity is eliminated within 24 hours and about 70 to 90% within 4 days (mainly as unchanged drug with small amounts of I-123 m-iodohippuric acid [I-123 MIHA], I-123 iodide, and I-123 m-iodobenzoic acid [I-123 MIBA]).

PRECAUTIONS TO CONSIDER

Pregnancy:

The possibility of pregnancy should be assessed in women of child-bearing potential. Clinical situations exist where the benefit to the patient and fetus, based on information derived from radiopharmaceutical use, outweighs the risks from fetal exposure to radiation. In these situations, the physician should use discretion and reduce the administered activity to the lowest possible amount.

Breast-feeding:

It is not known whether I-123 MIBG is distributed into breast milk. However, this preparation may be contaminated with free radioiodide, which may be distributed into breast milk. It has been recommended that, after administration of a radiopharmaceutical, nursing be resumed only after the infant's ingested effective dose equivalent (EDE) is below 1 mSv (100 mrem). A method to calculate the EDE has been proposed based on the effective half-life of the radionuclide, the activity administered to the mother, the fraction of administered activity ingested by the infant, and the total body effective dose to the newborn infant per unit of activity ingested. According to this method, it has been estimated that, for sodium iodide I-123, the time period required is 3 days with administration of an uncontaminated preparation, 40 days with a preparation contaminated with I-124, and 340 days for a preparation contaminated with I-125. Because of the difficulty of maintaining the maternal milk supply for such an extended period of time, complete cessation of nursing is usually recommended for all radioiodines, except for uncontaminated I-123.

Pediatrics:

When I-123MIBG is used in children, the diagnostic benefit should be judged to outweigh the potential risk of radiation.

DRUG INTERACTIONS AND/OR RELATED PROBLEMS

The following drug interactions and/or related problems have been selected on the basis of their potential clinical significance (possible mechanism in parentheses where appropriate)—not necessarily inclusive (» = major clinical significance):

» Amphetamines or

» Antidepressants, tricyclic or

» Bretylium or

» Calcium channel blocking agents or

» Cocaine or

» Guanethidine or

» Haloperidol or

» Labetalol or

» Loxapine or

» Metaraminol or

» Phenothiazines or

» Reserpine or

» Sympathomimetics or

» Thiothixene (these medications may interfere with the uptake of I-123 or I-131 MIBG; although the ideal time to stop treatment with potential interacting medicines is 1 week prior to administration of I-123 or I-131 MIBG, the following withdrawal periods are usually recommended based on the individual half-life of each medication: 24 hours for bretylium, cocaine, and metaraminol; 48 hours for amphetamines, calcium channel blocking agents, guanethidine, haloperidol, loxapine, tricyclic antidepressants, phenothiazines, sympathomimetics, and thiothixene; 72 hours for labetalol and reserpine) Phenoxybenzamine (although usual doses of phenoxybenzamine do not interfere with I-123 or I-131MIBG uptake, when given in high doses necessary to control blood pressure in patients with pheochromocytomas or paragangliomas preparing for surgery, tumor uptake of I-123 or I-131 MIBG may be suppressed resulting in false-negative studies)

SIDE/ADVERSE EFFECTS

At present, there are no known side/adverse effects associated with the use of diagnostic dosages of I-123 MIBG.

PREPARATION FOR THIS TEST

Special preparatory instructions may apply; patient should inquire in advance.

Administration of potassium iodide or Lugol’s solution one day before administration of I-123MIBG and for 6 days after administration to prevent or reduce thyroid uptake of radioiodide contaminant.

GENERAL DOSAGE INFORMATION

Radiopharmaceuticals are to be administered only by or under the supervision of physicians who have had extensive training in the safe use and handling of radioactive materials and who are authorized by the Nuclear Regulatory Commission (NRC) or the appropriate State agency, if required, or, outside the U.S., the appropriate authority. To minimize uptake of radioactive iodine by the thyroid, potassium iodide (SSKI, 60 mg twice a day) or Lugol's solution (1 drop three times a day) may be used, beginning at least 24 hours before and continuing for 6 days after administration of I-123 MIBG.

Safety considerations for handling this radiopharmaceutical:

Improper handling of this radiopharmaceutical may cause radioactive contamination. Guidelines for handling radioactive material have been prepared by scientific, professional, state, federal, and international bodies and are available to the specially qualified and authorized users who have access to radiopharmaceuticals.

IOBENGUANE I-123 INJECTION

Usual adult administered activity for diagnosis of tumors or medullary disease:

Intravenous, 370 megabecquerels (10 millicuries) of I-123 mIBG, with a minimum specific activity of 740 megabecquerels to 1.3 gigabecquerels (20 to 35.6 millicuries) per mg (at time of calibration), administered over a period of fifteen to thirty seconds.

Usual pediatric administered activity for diagnosis of tumors or medullary disease:

In children up to 18 years of age, dosage must be individualized by physician.

Usual geriatric administered activity:

See usual adult administered activity.

Thank you,

AnazaoHealth Corporation